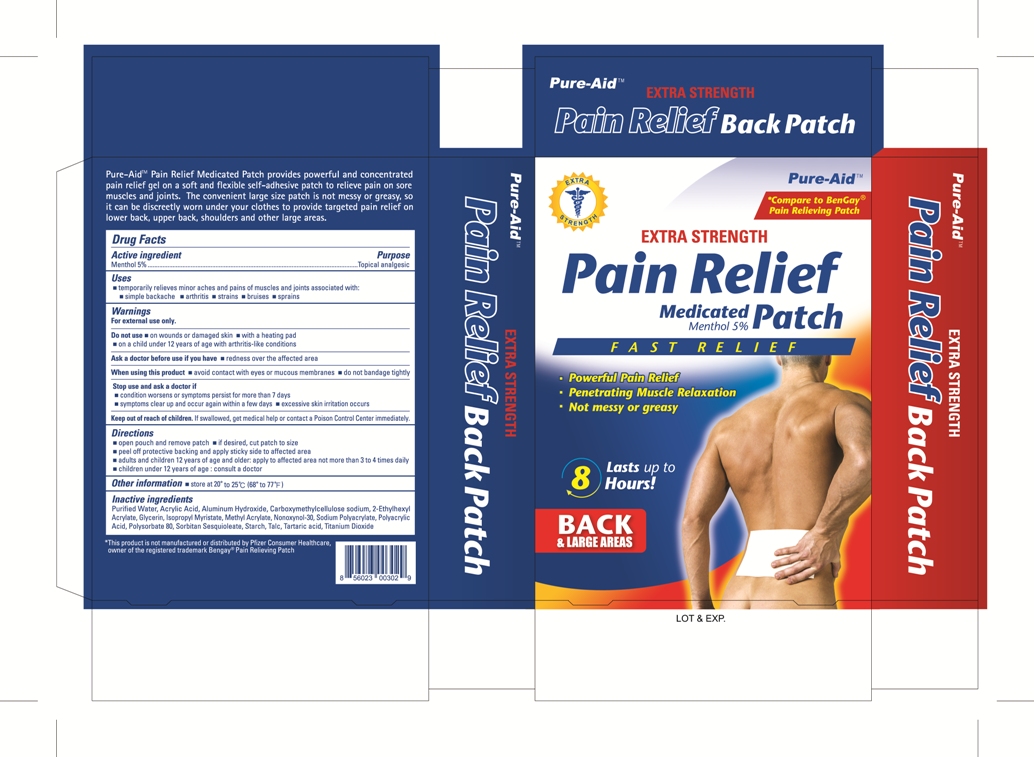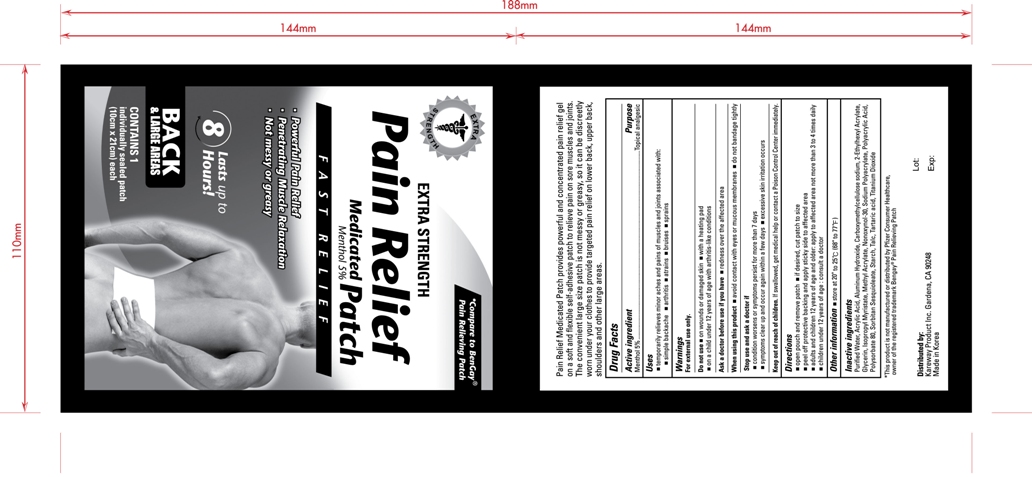 DRUG LABEL: Medicated Pain Relief
NDC: 67510-0302 | Form: PATCH
Manufacturer: Kareway Product, Inc.
Category: otc | Type: HUMAN OTC DRUG LABEL
Date: 20110907

ACTIVE INGREDIENTS: MENTHOL 428.5 mg/1 1
INACTIVE INGREDIENTS: WATER; ACRYLIC ACID; ALUMINUM HYDROXIDE; CARBOXYMETHYLCELLULOSE SODIUM; GLYCERIN; ISOPROPYL MYRISTATE; METHYL ACRYLATE; NONOXYNOL-30; POLYSORBATE 80; SORBITAN SESQUIOLEATE; TALC; TARTARIC ACID; TITANIUM DIOXIDE

Drug Facts

Active Ingredient

Menthol 5%

Purpose

Topical analgesic

Uses

- temporarily relieves minor aches and pains of muscles and joints associated with:
-
  - simple backache
-
  - arthritis
-
  - bruises
-
  - sprains

Warnings

For external use only

Do not use

- on wounds or damaged skin
- with a heating pad
- on a child under 12 years of age with arthritis-like conditions

Ask a doctor before using if you have

- redness over the affected area

When using this product

- avoid contact with eyes or mucous membranes
- do not bandage tightly

Stop use and ask a doctor if

- condition worsens or symptoms persist for more than 7 days
- symptoms clear up and occur again within a few days
- excessive skin irritation occurs

Keep out of reach of children.

If swallowed, get medical help or contact a Poison Control Center immediately.

Directions

- open pouch and remove patch
- if desired, cut patch to size
- peel off protective backing and apply sticky side to affected area
- adults and children 12 years of age and older: apply to affected area not more than 3 to 4 times daily
- children under 12 years of age: consult a doctor

Other information

- store at 20° to 25°C (68°F to 77°F)

Inactive ingredients

Purified Water, Acrylic Acid, Aluminum Hydroxide, Carboxymethylcellulose sodium, 2-Ethylhexyl Acrylate, Glycerin, Isopropyl Myristate, Methyl Acrylate, Nonoxymol-30, Sodium Polyacrylate, Polyacrylic Acid, Polysorbate 80, Sorbitan Sesquioleate, Starch, Talc, Tartaric acid, Titanium Dioxide

package label

Pain Relieving Patch, 4pk

----------------------------------------------------------------------------------------------------------------------------------------------------------------------------------------------------------------------------------------------------------------------------------------------------------------------------------------------------------------------------------

Bulk Patch